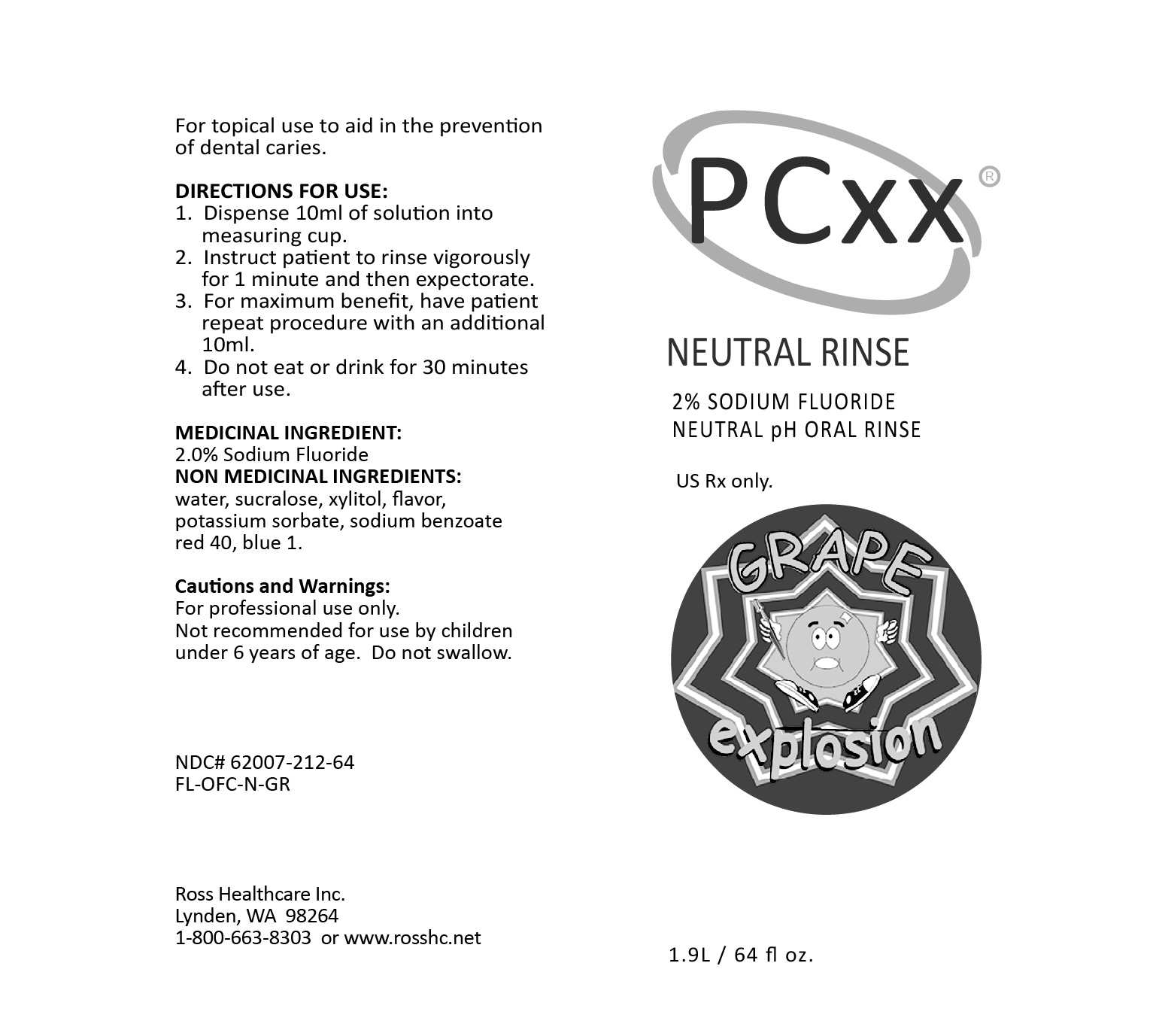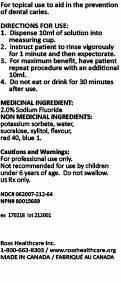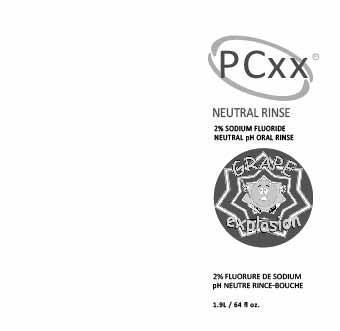 DRUG LABEL: PCXX NEUTRAL RNS GRAPE
NDC: 62007-212 | Form: RINSE
Manufacturer: Ross Healthcare Inc.
Category: prescription | Type: HUMAN PRESCRIPTION DRUG LABEL
Date: 20251106

ACTIVE INGREDIENTS: SODIUM FLUORIDE 2 mg/1 mL

PCXX NEUTRAL RNS GRAPE